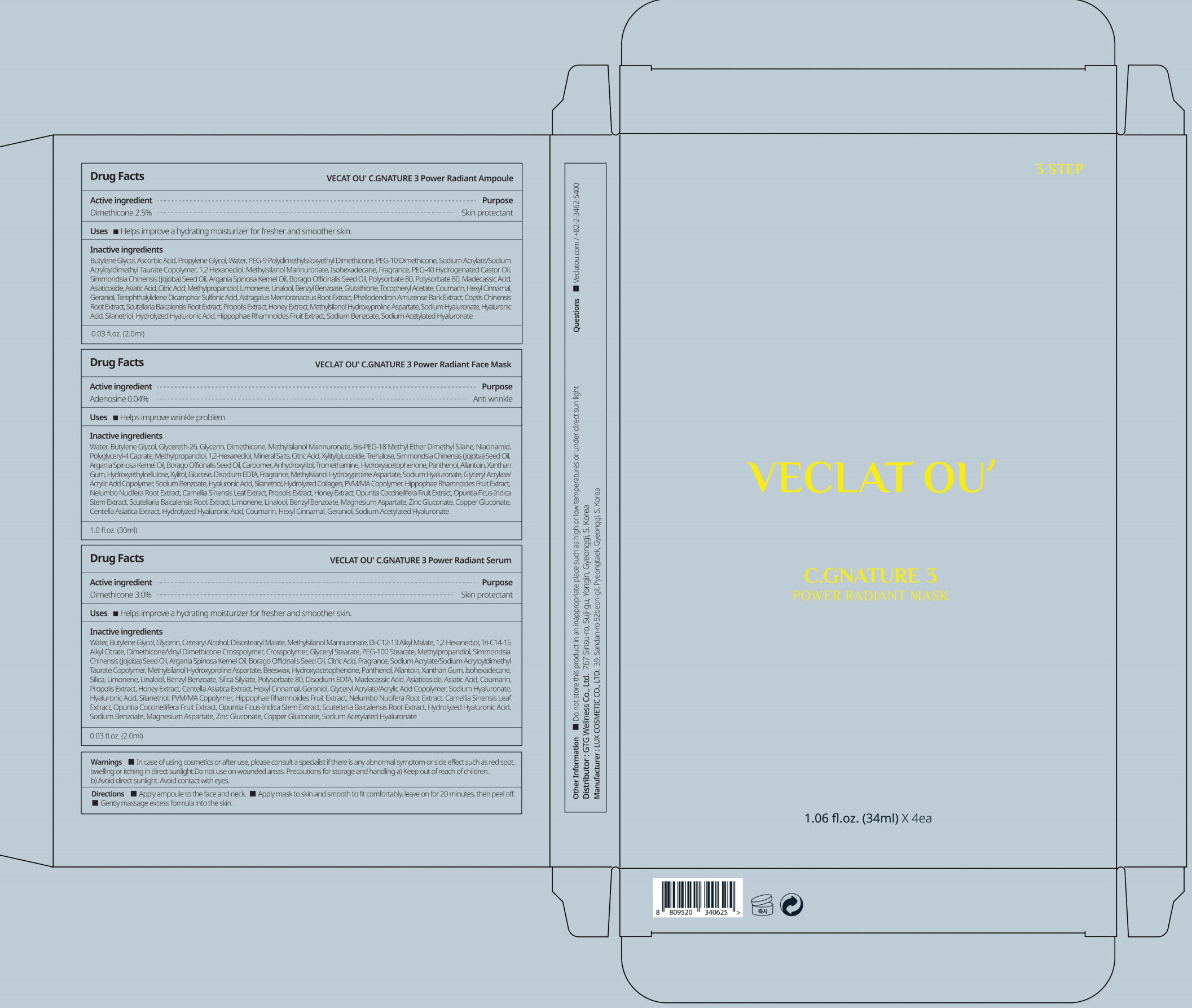 DRUG LABEL: VECLAT OU C.GNATURE 3 Power Radiant Ampoule
NDC: 71080-0029 | Form: LIQUID
Manufacturer: GTG WELLNESS CO., LTD.
Category: otc | Type: HUMAN OTC DRUG LABEL
Date: 20211129

ACTIVE INGREDIENTS: Dimethicone 2.5 g/100 mL
INACTIVE INGREDIENTS: Water; Butylene Glycol; Ascorbic Acid; Propylene Glycol

ACTIVE INGREDIENT

Dimethicone 2.5%

INACTIVE INGREDIENTS

Butylene Glycol, Ascorbic Acid, Propylene Glycol, Water, PEG-9 Polydimethylsiloxyethyl Dimethicone, PEG-10 Dimethicone, Sodium Acrylate/Sodium Acryloyldimethyl Taurate Copolymer, 1,2 Hexanediol, Methylsilanol Mannuronate, Isohexadecane, Fragrance, PEG-40 Hydrogenated Castor Oil, Simmondsia Chinensis (Jojoba) Seed Oil, Argania Spinosa Kernel Oil, Borago Officinalis Seed Oil, Polysorbate 80, Polysorbate 80, Madecassic Acid, Asiaticoside, Asiatic Acid, Citric Acid, Methylpropandiol, Limonene, Linalool, Benzyl Benzoate, Glutathione, Tocopheryl Acetate, Coumarin, Hexyl Cinnamal, Geraniol, Terephthalylidene Dicamphor Sulfonic Acid, Astragalus Membranaceus Root Extract, Phellodendron Amurense Bark Extract, Coptis Chinensis Root Extract, Scutellaria Baicalensis Root Extract, Propolis Extract, Honey Extract, Methylsilanol Hydroxyproline Aspartate, Sodium Hyaluronate, Hyaluronic Acid, Silanetriol, Hydrolyzed Hyaluronic Acid, Hippophae Rhamnoides Fruit Extract, Sodium Benzoate, Sodium Acetylated Hyaluronate

PURPOSE

Skin protectant

WARNINGS

In case of using cosmetics or after use, please consult a specialist if there is any abnormal symptom or side effect such as red spot, swelling or itching in direct sunlight.
Do not use on wounded areas.
Precautions for storage and handling
a) Keep out of reach of children.
b) Avoid direct sunlight.
Avoid contact with eyes.

KEEP OUT OF REACH OF CHILDREN

Uses

■ Helps improve a hydrating moisturizer for fresher and smoother skin.

Directions

■ Apply ampoule to the face and neck.
■ Apply mask to skin and smooth to fit comfortably, leave on for 20 minutes, then peel off.
■ Apply serum to the entire face and neck.

Other information

■ Do not store this product in an inappropriate place such as high or low temperatures or under direct sun light

Questions

■ Veclatou.com / +82-2-3462-5400